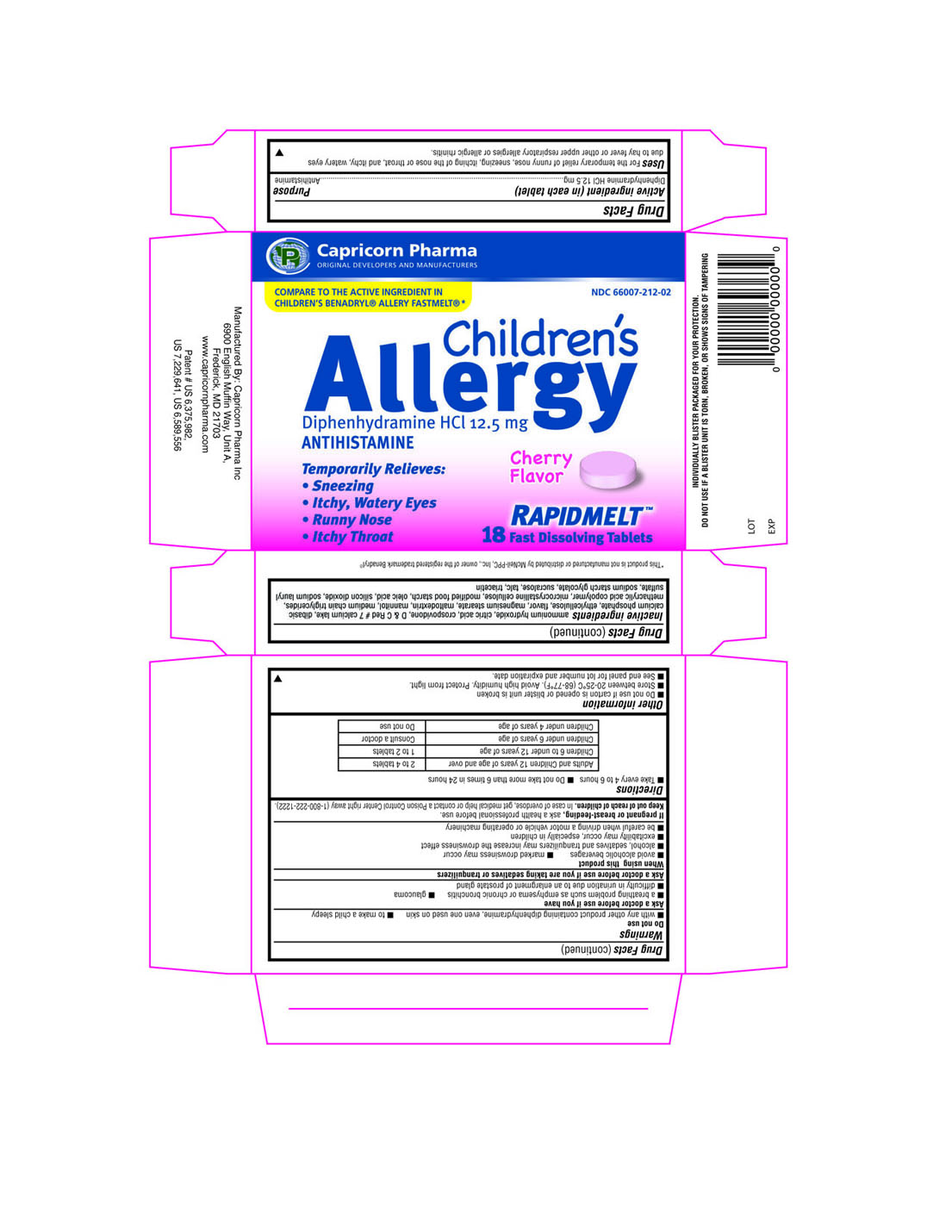 DRUG LABEL: Childrens Allergy
NDC: 66007-212 | Form: TABLET
Manufacturer: Capricorn Pharma Inc.
Category: otc | Type: HUMAN OTC DRUG LABEL
Date: 20101004

ACTIVE INGREDIENTS: DIPHENHYDRAMINE HYDROCHLORIDE 12.5 mg/1 1
INACTIVE INGREDIENTS: ETHYLCELLULOSE; ANHYDROUS CITRIC ACID; CROSPOVIDONE; DIBASIC CALCIUM PHOSPHATE DIHYDRATE; MAGNESIUM STEARATE; MALTODEXTRIN; MANNITOL; METHACRYLIC ACID - ETHYL ACRYLATE COPOLYMER (1:1) TYPE A; CELLULOSE, MICROCRYSTALLINE; MODIFIED CORN STARCH (1-OCTENYL SUCCINIC ANHYDRIDE); SILICON DIOXIDE; SODIUM LAURYL SULFATE; SODIUM STARCH GLYCOLATE TYPE A POTATO; SUCRALOSE; TALC; TRIACETIN; AMMONIA; CAPRYLIC/CAPRIC MONO/DIGLYCERIDES; OLEIC ACID

Drug Facts

Active ingredient (in each tablet)

Diphenhydramine HCl 12.5mg

Purpose

Antihistamine

INDICATIONS AND USAGE

Uses For the temporary relief of runny nose, sneezing, itching of the nose or throat, and itchy, watery eyes due to hay fever or other upper respiratory allergies or allergic rhinitis.

Warnings

Do not use

- with any other product containing Diphenhydramine, even one used on skin
- to make a child sleepy

Ask a doctor before use if you have

- a breathing problem such as emphysema or chronic bronchitis
- glaucoma
- difficulty in urination due to an enlargement of prostate gland

When using this product

- Avoid alcoholic beverages
- Marked drowsiness may occur
- Alcohol, sedatives and tranquilizers may increase the drowsiness effect
- Excitability may occur, especially in children
- Be careful when driving a motor vehicle or operating machinery

Keep out of reach of children.

In case of overdose, get medical help or contact a Poison Center right away (1-800-222-1222).

Directions

- Take every 4 to 6 hours
- Do not take more than 6 times in 24 hours

Adults and Children 12 years of age and over | 2 to 4 tablets
Children 6 to under 12 years of age | 1 to 2 tablets
Children under 6 years of age | Consult a doctor
Children under 4 years of age | Do not use

Other Information

- Do not use if carton is opened or blister unit is broken
- Store between 20-25°C (68-77°F). Avoid high humidity. Protect from light.
- See end panel for lot number and expiration date.

Inactive ingredients

aqueous ethyl cellulose dispersion, citric acid, crospovidone, D and C Red # 7 calcium lake, dibasic calcium phosphate, flavor, magnesium stearate, maltodextrin, mannitol, methacrylic acid copolymer, microcrystalline cellulose, modified food starch, silicon dioxide, sodium lauryl sulfate, sodium starch glycolate, sucralose, talc, triacetin

Principal Display Panel

Capricorn Pharma

ORIGINAL DEVELOPERS AND MANUFACTURERS

NDC 66007-212-02

COMPARE TO THE ACTIVE INGREDIENT IN CHILDREN'S BENADRYL ALLERGY FASTMELT

Children's Allergy

Diphenhydramine HCl 12.5mg

ANTIHISTAMINE

Temporarily Relieves:

- Sneezing
- Itchy, Watery Eyes
- Runny Nose
- Itchy Throat

Cherry Flavor

RAPIDMELT
18 Fast Dissolving Tablets